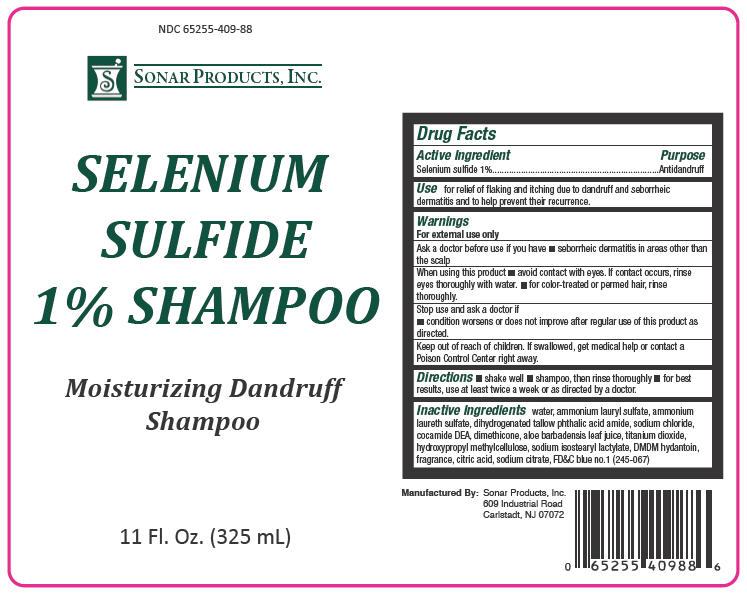 DRUG LABEL: Selenium sulfide
NDC: 65255-409 | Form: SHAMPOO
Manufacturer: Sonar Products, Inc
Category: otc | Type: HUMAN OTC DRUG LABEL
Date: 20120131

ACTIVE INGREDIENTS: SELENIUM SULFIDE 10 mg/1 mL
INACTIVE INGREDIENTS: WATER; COCO DIETHANOLAMIDE; DIHYDROGENATED TALLOW PHTHALIC ACID AMIDE; HYPROMELLOSES; DIMETHICONE; DMDM HYDANTOIN; AMMONIUM LAURYL SULFATE; SODIUM LAURETH SULFATE; SODIUM ISOSTEAROYL LACTYLATE; SODIUM CHLORIDE; CITRIC ACID MONOHYDRATE; ALOE VERA LEAF; TITANIUM DIOXIDE; SODIUM CITRATE; FD&C BLUE NO. 1

Selenium Sulfide 1% Moisturizing Dandruff Shampoo

Drug Facts

Active Ingredient

Selenium sulfide 1%

Purpose

Antidandruff

Use

for relief of flaking and itching due to dandruff and seborrheic dermatitis and to help prevent their recurrence.

Warnings

For external use only

Ask a doctor before use if you have

- seborrheic dermatitis in areas other than the scalp

When using this product

- avoid contact with eyes. If contact occurs, rinse eyes thoroughly with water.
- for color-treated or permed hair, rinse thoroughly.

Stop use and ask a doctor if

- condition worsens or does not improve after regular use of this product as directed.

Keep out of reach of children. If swallowed, get medical help or contact a Poison Control Center right away.

Directions

- shake well
- shampoo, then rinse thoroughly
- for best results, use at least twice a week or as directed by a doctor.

Inactive Ingredients

water, ammonium lauryl sulfate, ammonium laureth sulfate, dihydrogenated tallow phthalic acid amide, sodium chloride, cocamide DEA, dimethicone, aloe barbadensis leaf juice, titanium dioxide, hydroxypropyl methylcellulose, sodium isostearyl lactylate, DMDM hydantoin, fragrance, citric acid, sodium citrate, FD&C blue no.1 (245-067)

Manufactured By:
Sonar Products, Inc.
609 Industrial Road
Carlstadt, NJ 07072

PRINCIPAL DISPLAY PANEL - 325 mL Bottle Label

NDC 65255-409-88

SONAR PRODUCTS, INC.

SELENIUM
SULFIDE
1% SHAMPOO

Moisturizing Dandruff
Shampoo

11 Fl. Oz. (325 mL)